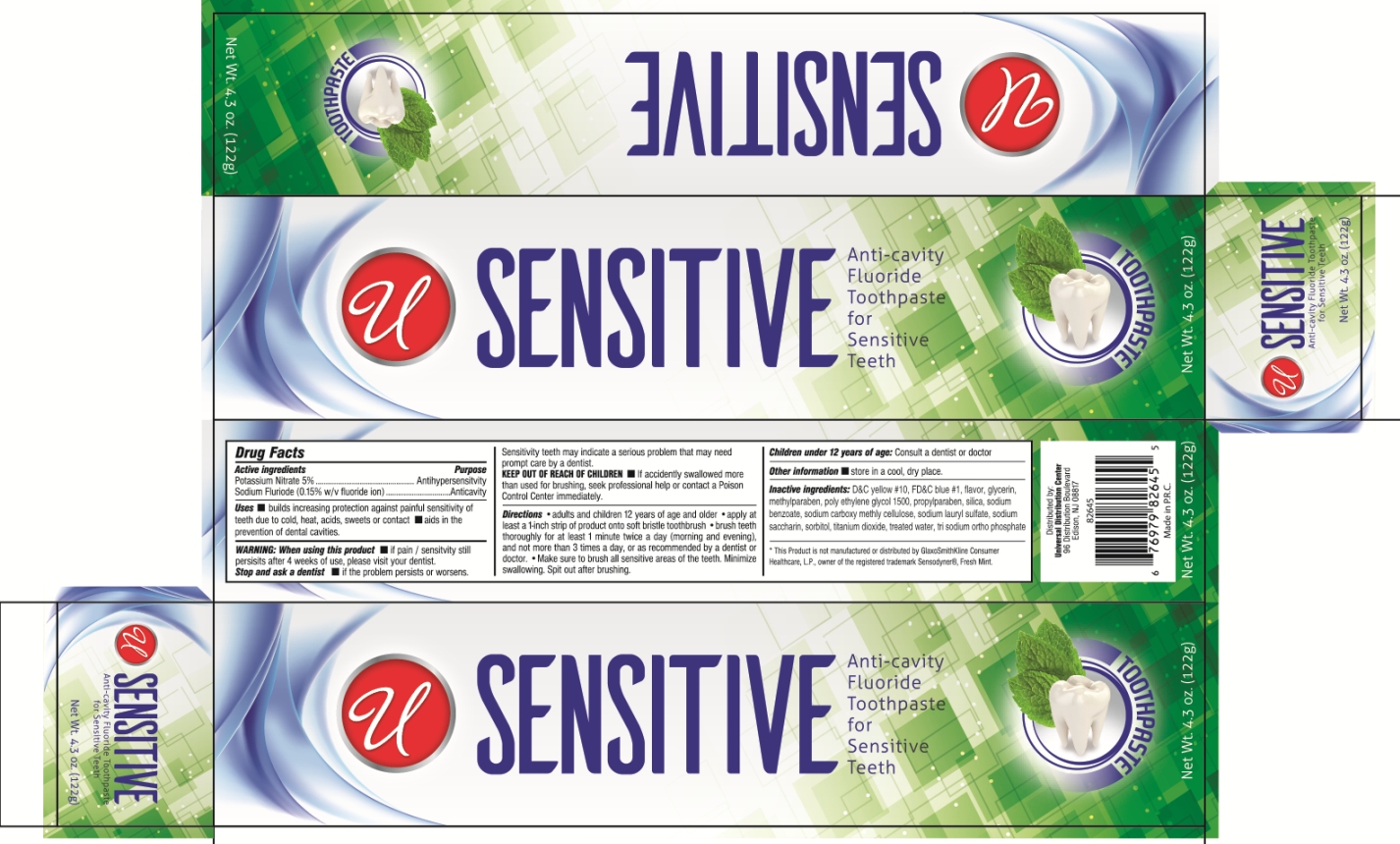 DRUG LABEL: SENSITIVE ANTI-CAVITY
NDC: 52000-037 | Form: PASTE
Manufacturer: Universal Distribution Center LLC
Category: otc | Type: HUMAN OTC DRUG LABEL
Date: 20170621

ACTIVE INGREDIENTS: POTASSIUM NITRATE 50 mg/1 g; SODIUM FLUORIDE 1.5 mg/1 g
INACTIVE INGREDIENTS: D&C YELLOW NO. 10; FD&C BLUE NO. 1; GLYCERIN; METHYLPARABEN; POLYETHYLENE GLYCOL 1500; PROPYLPARABEN; SILICON DIOXIDE; SODIUM BENZOATE; CARBOXYMETHYLCELLULOSE SODIUM; SODIUM LAURYL SULFATE; SACCHARIN SODIUM; SORBITOL; TITANIUM DIOXIDE

SENSITIVE ANTI-CAVITY FLUORIDE TOOTHPASTE

Active Ingredients

Potassium Nitrate 5%

Sodium Fluoride (0.15% w/v fluoride ion)

Purpose

Antihypersensitivity

Anticavity

Uses

- builds increasing protection against painful sensitivity of teeth due to cold, heat, acids, sweets or contact.
- aids in the prevention of dental cavities.

Warning

When using this product

- if pain\ sensitivity still persists after 4 weeks of use, please visit your dentist.

Stop and ask a dentist

- if the problem persists or worsens.

Sensitivity teeth may indicate a serious problem that may need prompt care by a dentist.

Keep out of reach of children

- If accidentally swallowed more than used for brushing, seek professional help or contact a Poison Control Center immediately.

Directions

Adults and Children 12 years of age and older:

- apply at least a 1-inch strip of product onto soft bristle toothbrush
- brush teeth thoroughly for at least 1 minute twice a day (morning and evening), and not more than 3 times day, or as recommended by a dentist or doctor.
- make sure to brush all sensitive areas of the teeth. Minimize swallowing. Spit out after brushing.

Children under 12 years of age: Consult a dentist or doctor.

Other information

- store in a cool, dry place.

Inactive Ingredients

D&C yellow#10, FD&C blue#1, flavor, glycerin, methylparaben, poly ethylene glycol 1500, propylparaben, silica, sodium benzoate, sodium carboxy methyl cellulose, sodium lauryl sulfate, sodium saccharin, sorbitol, titanium dioxide, treated water, tri sodium ortho phosphate.

PACKAGE LABEL

PRINCIPAL DISPLAY PANEL

SENSITIVE ANTI-CAVITY FLUORIDE TOOTHPASTE